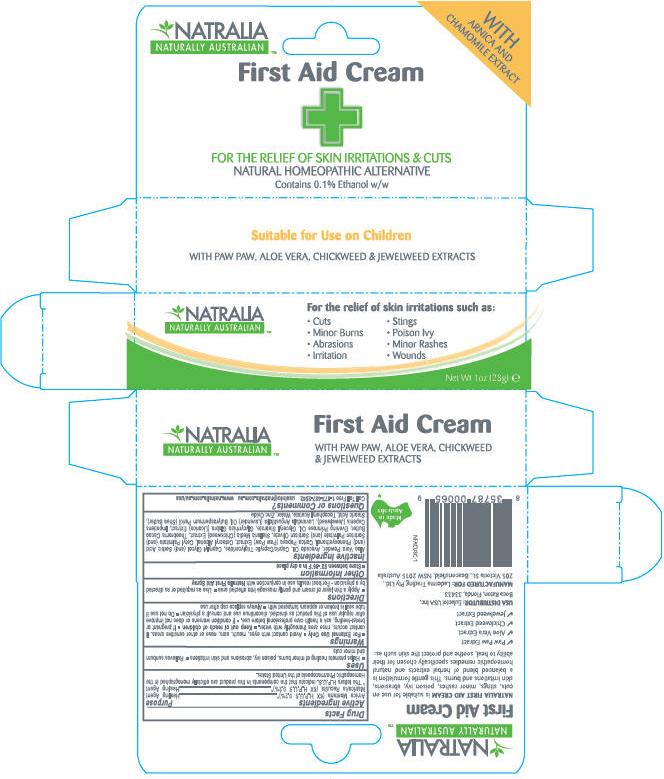 DRUG LABEL: FLEXITOL FIRST AID
NDC: 43251-3363 | Form: CREAM
Manufacturer: Laderma Trading Pty Ltd
Category: otc | Type: HUMAN OTC DRUG LABEL
Date: 20100129

ACTIVE INGREDIENTS: ARNICA MONTANA FLOWER 2 mg/1 g; CHAMOMILE 2 mg/1 g

NATRALIA
NATURALLY AUSTRALIAN ™
First Aid Cream

Drug Facts

ACTIVE INGREDIENT

Active ingredients | Purpose
Arnica Montana (6X H.P.U.S 0.2%) [The letters H.P.U.S. indicate that the components in this product are officially monographed in the Homeopathic Pharmacopoeia of the United States.] | Healing Agent
Matricaria Recutita (6X H.P.U.S 0.2%) | Healing Agent

Uses

- Helps promote healing of minor burns, poison ivy, abrasions and skin irritations
- Relieves sunburn and minor cuts

Warnings

- For External Use Only
- Avoid contact with eyes, mouth, ears, nose or other sensitive areas. If contact occurs, rinse area thoroughly with water.
- Keep out of reach of children
- If pregnant or breast-feeding, ask a health care professional before use.
- If condition worsens or does not improve after regular use of this product as directed, discontinue use and consult a physician
- Do not use if tube seal is broken or appears tampered with
- Always replace cap after use

Directions

- Apply a thin layer of cream and gently massage into affected area
- Use as required or as directed by a physician
  - For best results use in conjunction with Natralia First Aid Spray

Other Information

- Store between 50°-86°F in a dry place

Inactive Ingredients

Aloe Vera Powder, Avocado Oil, Capric/Caprylic Triglycerides, Caprylyl Glycol (and) Sorbic Acid (and) Phenoxyethanol, Carica Papaya (Paw Paw) Extract, Cetearyl Alcohol, Cetyl Palmitate (and) Sorbitan Palmitate (and) Sorbitan Olivate, Stellaria Media (Chickweed) Extract, Theobroma Cacao Butter, Evening Primrose Oil, Glyceryl Stearate, Glycyrrhiza Glabra (Licorice) Extract, Impatiens Cepenis (Jewelweed), Lavandula Angustifolia (Lavender) Oil, Butyrospermum Parkii (Shea Butter), Stearic Acid, Tocopheryl Acetate, Water, Zinc Oxide

Questions or Comments?

Call Toll Free 1-877-687-2542 usainfo@natrlia.com.au www.natralia.com.au/usa

Principal Display Panel - 1 oz Carton

NATRALIA
NATURALLY AUSTRALIAN™

For the relief of skin irritations such as:

- Cuts
- Minor Burns
- Abrasions
- Irritation

- Stings
- Poison Ivy
- Minor Rashes
- Wounds

Net Wt 1oz (28g) e